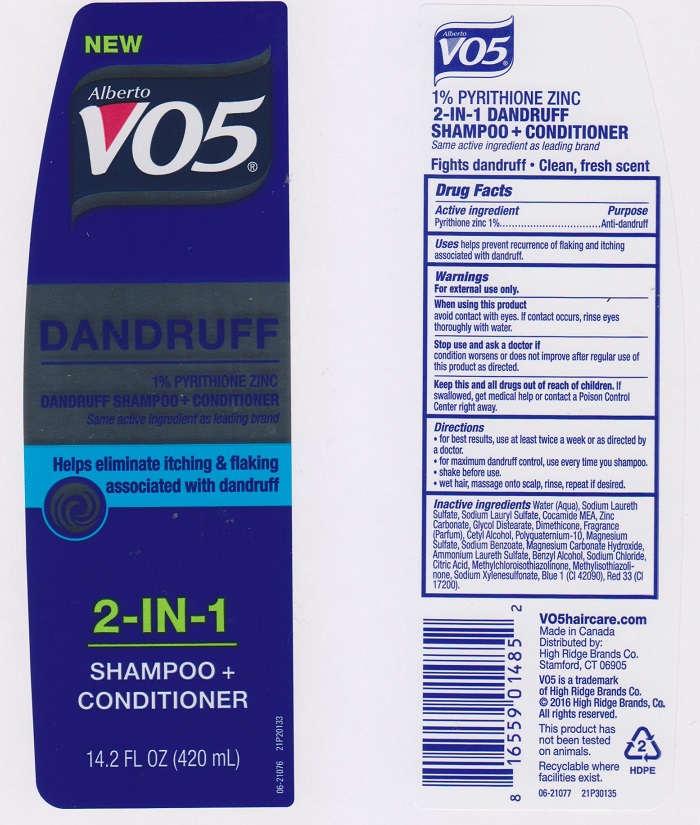 DRUG LABEL: Alberto VO5 2 in 1 Dandruff
NDC: 63148-434 | Form: LIQUID
Manufacturer: APOLLO HEALTH AND BEAUTY CARE
Category: otc | Type: HUMAN OTC DRUG LABEL
Date: 20160119

ACTIVE INGREDIENTS: PYRITHIONE ZINC 10 mg/1 mL
INACTIVE INGREDIENTS: WATER; SODIUM LAURETH SULFATE; SODIUM LAURYL SULFATE; COCO MONOETHANOLAMIDE; ZINC CARBONATE; GLYCOL DISTEARATE; DIMETHICONE; CETYL ALCOHOL; POLYQUATERNIUM-10 (400 CPS AT 2%); MAGNESIUM SULFATE; SODIUM BENZOATE; MAGNESIUM CARBONATE HYDROXIDE; AMMONIUM LAURETH-3 SULFATE; BENZYL ALCOHOL; SODIUM CHLORIDE; CITRIC ACID MONOHYDRATE; METHYLCHLOROISOTHIAZOLINONE; METHYLISOTHIAZOLINONE; SODIUM XYLENESULFONATE; FD&C BLUE NO. 1; D&C RED NO. 33

DRUG FACTS

Active ingredient

Pyrithione Zinc 1%

Purpose

Anti-dandruff

Uses

helps prevent recurrence of flaking and itching associated with dandruff.

Warnings

For external use only.

When using this product

avoid contact with eyes. If contact occurs, rinse eyes thoroughly with water.

Stop use and ask a doctor if

condition worsens or does not improve after regular use of this product as directed.

Keep this and all drugs out of reach of children.

If swallowed, get medical help or contact a Poison Control Center right away.

Directions

- for best results, use at least twice a week or as directed by a doctor.
- for maximum dandruff control, use every time you shampoo.
- shake before use.
- wet hair, massage onto scalp, rinse, repeat if desired.

Inactive ingredients

Water (Aqua), Sodium Laureth Sulfate, Sodium Lauryl Sulfate, Cocamide MEA, Zinc Carbonate, Glycol Distearate, Dimethicone, Fragrance (Parfum), Cetyl Alcohol, Polyquaternium-10, Magnesium Sulfate, Sodium Benzoate, Magnesium Carbonate Hydroxide, Ammonium Laureth Sulfate, Benzyl Alcohol, Sodium Chloride, Citric Acid, Methylchloroisothiazolinone, Methylisothiazolinone, Sodium Xylenesulfonate, Blue 1 (CI 42090), Red 33 (CI 17200).